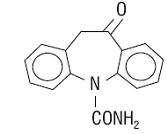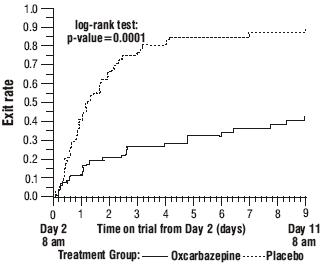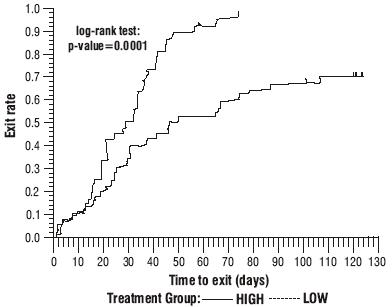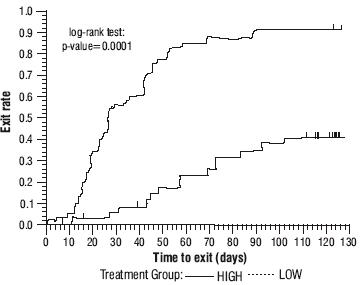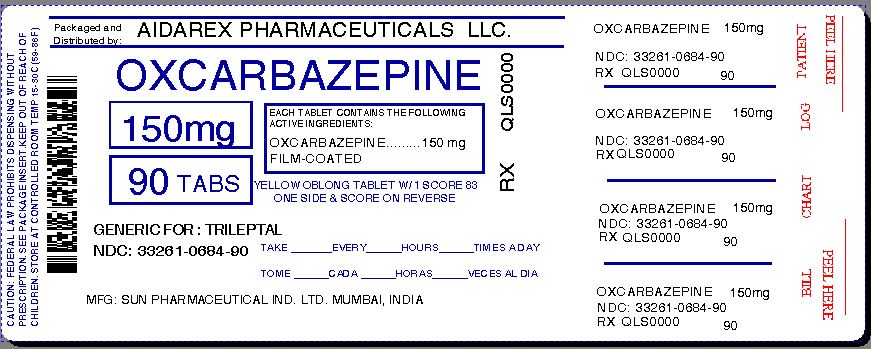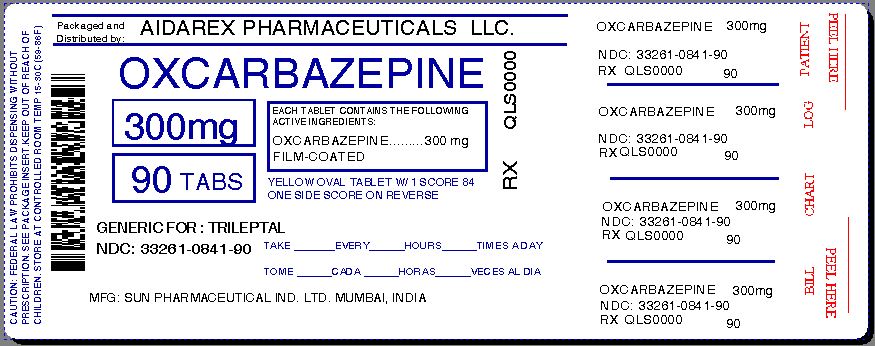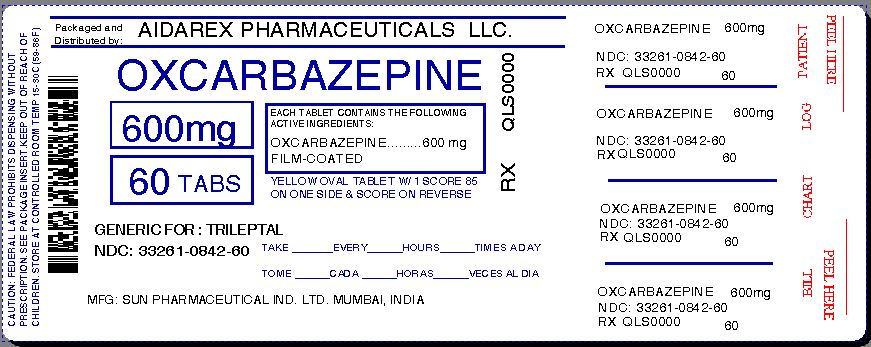 DRUG LABEL: Oxcarbazepine
NDC: 33261-684 | Form: TABLET, FILM COATED
Manufacturer: Aidarex Pharmaceuticals LLC
Category: prescription | Type: HUMAN PRESCRIPTION DRUG LABEL
Date: 20140121

ACTIVE INGREDIENTS: OXCARBAZEPINE 150 mg/1 1
INACTIVE INGREDIENTS: SILICON DIOXIDE; POVIDONE K30; POLYETHYLENE GLYCOLS; CROSCARMELLOSE SODIUM; CROSPOVIDONE; CELLULOSE, MICROCRYSTALLINE; SODIUM STEARYL FUMARATE; HYPROMELLOSES; POLYSORBATE 80; TITANIUM DIOXIDE; FERRIC OXIDE YELLOW

Oxcarbazepine Tablets

DESCRIPTION

Oxcarbazepine is an antiepileptic drug available as 150 mg, 300 mg and 600 mg film-coated tablets for oral administration. Oxcarbazepine is 10,11-Dihydro-10-oxo-5H-dibenz[b,f]azepine-5-carboxamide, and its structural formula is

Oxcarbazepine is a white to faintly orange crystalline powder. It is slightly soluble in chloroform, dichloromethane, acetone, and methanol and practically insoluble in ethanol, ether and water. Its molecular weight is 252.27.

Oxcarbazepine film-coated tablets contain the following inactive ingredients: colloidal silicon dioxide, povidone, polyethylene glycol, croscarmellose sodium, microcrystalline cellulose, crospovidone, sodium stearyl fumarate, hypromellose, polysorbate 80, titanium dioxide and yellow iron oxide.

CLINICAL PHARMACOLOGY

Mechanism of Action

The pharmacological activity of oxcarbazepine is primarily exerted through the 10-monohydroxy metabolite (MHD) of oxcarbazepine (see Metabolism and Excretion subsection). The precise mechanism by which oxcarbazepine and MHD exert their antiseizure effect is unknown; however, in vitro electrophysiological studies indicate that they produce blockade of voltage-sensitive sodium channels, resulting in stabilization of hyperexcited neural membranes, inhibition of repetitive neuronal firing, and diminution of propagation of synaptic impulses. These actions are thought to be important in the prevention of seizure spread in the intact brain. In addition, increased potassium conductance and modulation of high-voltage activated calcium channels may contribute to the anticonvulsant effects of the drug. No significant interactions of oxcarbazepine or MHD with brain neurotransmitter or modulator receptor sites have been demonstrated.

Pharmacodynamics

Oxcarbazepine and its active metabolite (MHD) exhibit anticonvulsant properties in animal seizure models. They protected rodents against electrically induced tonic extension seizures and, to a lesser degree, chemically induced clonic seizures, and abolished or reduced the frequency of chronically recurring focal seizures in Rhesus monkeys with aluminum implants. No development of tolerance (i.e., attenuation of anticonvulsive activity) was observed in the maximal electroshock test when mice and rats were treated daily for five days and four weeks, respectively, with oxcarbazepine or MHD.

Pharmacokinetics

Following oral administration of oxcarbazepine tablets, oxcarbazepine is completely absorbed and extensively metabolized to its pharmacologically active 10-monohydroxy metabolite (MHD). The half-life of the parent is about two hours, while the half-life of MHD is about nine hours, so that MHD is responsible for most antiepileptic activity.

Based on MHD concentrations, oxcarbazepine tablets and suspension were shown to have similar bioavailability.

After single-dose administration of oxcarbazepine tablets to healthy male volunteers under fasted conditions, the median tmax was 4.5 (range 3 to 13) hours.

In a mass balance study in people, only 2% of total radioactivity in plasma was due to unchanged oxcarbazepine, with approximately 70% present as MHD, and the remainder attributable to minor metabolites.

Effect of Food: Food has no effect on the rate and extent of absorption of oxcarbazepine from oxcarbazepine tablets. Therefore, oxcarbazepine tablets can be taken with or without food.

Steady-state plasma concentrations of MHD are reached within 2 to 3 days in patients when oxcarbazepine is given twice a day. At steady-state the pharmacokinetics of MHD are linear and show dose proportionality over the dose range of 300 to 2400 mg/day.

Distribution

The apparent volume of distribution of MHD is 49L.

Approximately 40% of MHD is bound to serum proteins, predominantly to albumin. Binding is independent of the serum concentration within the therapeutically relevant range. Oxcarbazepine and MHD do not bind to alpha-1-acid glycoprotein.

Metabolism and Excretion

Oxcarbazepine is rapidly reduced by cytosolic enzymes in the liver to its 10-monohydroxy metabolite, MHD, which is primarily responsible for the pharmacological effect of oxcarbazepine. MHD is metabolized further by conjugation with glucuronic acid. Minor amounts (4% of the dose) are oxidized to the pharmacologically inactive 10,11-dihydroxy metabolite (DHD).

Oxcarbazepine is cleared from the body mostly in the form of metabolites which are predominantly excreted by the kidneys. More than 95% of the dose appears in the urine, with less than 1% as unchanged oxcarbazepine. Fecal excretion accounts for less than 4% of the administered dose. Approximately 80% of the dose is excreted in the urine either as glucuronides of MHD (49%) or as unchanged MHD (27%); the inactive DHD accounts for approximately 3% and conjugates of MHD and oxcarbazepine account for 13% of the dose.

Special Populations

Hepatic Impairment

The pharmacokinetics and metabolism of oxcarbazepine and MHD were evaluated in healthy volunteers and hepatically-impaired subjects after a single 900 mg oral dose. Mild-to-moderate hepatic impairment did not affect the pharmacokinetics of oxcarbazepine and MHD. No dose adjustment for oxcarbazepine is recommended in patients with mild-to-moderate hepatic impairment. The pharmacokinetics of oxcarbazepine and MHD have not been evaluated in severe hepatic impairment and, therefore, caution should be exercised when dosing severely impaired patients.

Renal Impairment

There is a linear correlation between creatinine clearance and the renal clearance of MHD. When oxcarbazepine is administered as a single 300 mg dose in renally-impaired patients (creatinine clearance < 30 mL/min), the elimination half-life of MHD is prolonged to 19 hours, with a two-fold increase in AUC. Dose adjustment for oxcarbazepine is recommended in these patients (see PRECAUTIONS and DOSAGE AND ADMINISTRATION sections).

Pediatric Use

Weight-adjusted MHD clearance decreases as age and weight increases, approaching that of adults. The mean weight-adjusted clearance in children 2 years to <4 years of age is approximately 80% higher on average than that of adults. Therefore, MHD exposure in these children is expected to be about one-half that of adults when treated with a similar weight-adjusted dose. The mean weight-adjusted clearance in children 4 to 12 years of age is approximately 40% higher on average than that of adults. Therefore, MHD exposure in these children is expected to be about three-quarters that of adults when treated with a similar weight-adjusted dose. As weight increases, for patients 13 years of age and above, the weight-adjusted MHD clearance is expected to reach that of adults.

Geriatric Use

Following administration of single (300 mg) and multiple (600 mg/day) doses of oxcarbazepine to elderly volunteers (60 to 82 years of age), the maximum plasma concentrations and AUC values of MHD were 30% to 60% higher than in younger volunteers (18 to 32 years of age). Comparisons of creatinine clearance in young and elderly volunteers indicate that the difference was due to age-related reductions in creatinine clearance.

Gender

No gender-related pharmacokinetic differences have been observed in children, adults, or the elderly.

Race

No specific studies have been conducted to assess what effect, if any, race may have on the disposition of oxcarbazepine.

CLINICAL STUDIES

The effectiveness of oxcarbazepine as adjunctive and monotherapy for partial seizures in adults, and as adjunctive therapy in children aged 2 to 16 years was established in seven multicenter, randomized, controlled trials.

The effectiveness of oxcarbazepine as monotherapy for partial seizures in children aged 4 to 16 years was determined from data obtained in the studies described, as well as by pharmacokinetic/pharmacodynamic considerations.

Oxcarbazepine Monotherapy Trials

Four randomized, controlled, double-blind, multicenter trials, conducted in a predominately adult population, demonstrated the efficacy of oxcarbazepine as monotherapy. Two trials compared oxcarbazepine to placebo and two trials used a randomized withdrawal design to compare a high dose (2400 mg) with a low dose (300 mg) of oxcarbazepine, after substituting oxcarbazepine 2400 mg/day for one or more antiepileptic drugs (AEDs). All doses were administered on a BID schedule. A fifth randomized, controlled, rater-blind, multicenter study, conducted in a pediatric population, failed to demonstrate a statistically significant difference between low and high dose oxcarbazepine treatment groups.

One placebo-controlled trial was conducted in 102 patients (11 to 62 years of age) with refractory partial seizures who had completed an inpatient evaluation for epilepsy surgery. Patients had been withdrawn from all AEDs and were required to have 2 to 10 partial seizures within 48 hours prior to randomization. Patients were randomized to receive either placebo or oxcarbazepine given as 1500 mg/day on Day 1 and 2400 mg/day thereafter for an additional nine days, or until one of the following three exit criteria occurred: 1) the occurrence of a fourth partial seizure, excluding Day 1, 2) two new-onset secondarily generalized seizures, where such seizures were not seen in the one-year period prior to randomization, or 3) occurrence of serial seizures or status epilepticus. The primary measure of effectiveness was a between-group comparison of the time to meet exit criteria. There was a statistically significant difference in favor of oxcarbazepine (see Figure 1), p=0.0001.

Figure 1: Kaplan-Meier Estimates of Exit Rate by Treatment Group

The second placebo-controlled trial was conducted in 67 untreated patients (8 to 69 years of age) with newly-diagnosed and recent-onset partial seizures. Patients were randomized to placebo or oxcarbazepine, initiated at 300 mg BID and titrated to 1200 mg/day (given as 600 mg BID) in six days, followed by maintenance treatment for 84 days. The primary measure of effectiveness was a between-group comparison of the time to first seizure. The difference between the two treatments was statistically significant in favor of oxcarbazepine (see Figure 2), p=0.046.

Figure 2: Kaplan-Meier Estimates of First Seizure Event Rate by Treatment Group

A third trial substituted oxcarbazepine monotherapy at 2400 mg/day for carbamazepine in 143 patients (12 to 65 years of age) whose partial seizures were inadequately controlled on carbamazepine (CBZ) monotherapy at a stable dose of 800 to 1600 mg/day, and maintained this oxcarbazepine dose for 56 days (baseline phase). Patients who were able to tolerate titration of oxcarbazepine to 2400 mg/day during simultaneous carbamazepine withdrawal were randomly assigned to either 300 mg/day of oxcarbazepine or 2400 mg/day oxcarbazepine. Patients were observed for 126 days or until one of the following four exit criteria occurred: 1) a doubling of the 28-day seizure frequency compared to baseline, 2) a two-fold increase in the highest consecutive two-day seizure frequency during baseline, 3) a single generalized seizure if none had occurred during baseline, or 4) a prolonged generalized seizure. The primary measure of effectiveness was a between-group comparison of the time to meet exit criteria. The difference between the curves was statistically significant in favor of the oxcarbazepine 2400 mg/day group (see Figure 3), p=0.0001.

Figure 3: Kaplan-Meier Estimates of Exit Rate by Treatment Group

Another monotherapy substitution trial was conducted in 87 patients (11 to 66 years of age) whose seizures were inadequately controlled on one or two AEDs. Patients were randomized to either oxcarbazepine 2400 mg/day or 300 mg/day and their standard AED regimen(s) were eliminated over the first six weeks of double-blind therapy. Double-blind treatment continued for another 84 days (total double-blind treatment of 126 days) or until one of the four exit criteria described for the previous study occurred. The primary measure of effectiveness was a between-group comparison of the percentage of patients meeting exit criteria. The results were statistically significant in favor of the oxcarbazepine 2400 mg/day group (14/34; 41.2%) compared to the oxcarbazepine 300 mg/day group (42/45; 93.3%) (p<0.0001). The time to meeting one of the exit criteria was also statistically significant in favor of the oxcarbazepine 2400 mg/day group (see Figure 4), p=0.0001.

Figure 4: Kaplan-Meier Estimates of Exit Rate by Treatment Group

A monotherapy trial was conducted in 92 pediatric patients (1 month to 16 years of age) with inadequately-controlled or new-onset partial seizures. Patients were hospitalized and randomized to either oxcarbazepine 10 mg/kg/day or were titrated up to 40 to 60 mg/kg/day within three days while withdrawing the previous AED on the second day of oxcarbazepine therapy. Seizures were recorded through continuous video-EEG monitoring from Day 3 to Day 5. Patients either completed the 5-day treatment or met one of the two exit criteria: 1) three study-specific seizures (i.e., electrographic partial seizures with a behavioral correlate), 2) a prolonged study-specific seizure. The primary measure of effectiveness was a between-group comparison of the time to meet exit criteria in which the difference between the curves was not statistically significant (p=0.904). The majority of patients from both dose groups completed the 5-day study without exiting.

Although this study failed to demonstrate an effect of oxcarbazepine as monotherapy in pediatric patients, several design elements, including the short treatment and assessment period, the absence of a true placebo, and the likely persistence of plasma levels of previously administered AEDs during the treatment period, make the results uninterpretable. For this reason, the results do not undermine the conclusion, based on pharmacokinetic/pharmacodynamic considerations, that oxcarbazepine is effective as monotherapy in pediatric patients 4 years old and older.

Oxcarbazepine Adjunctive Therapy Trials

The effectiveness of oxcarbazepine as an adjunctive therapy for partial seizures was established in two multicenter, randomized, double-blind, placebo-controlled trials, one in 692 patients (15 to 66 years of age) and one in 264 pediatric patients (3 to 17 years of age), and in one multicenter, rater-blind, randomized, age-stratified, parallel-group study comparing two doses of oxcarbazepine in 128 pediatric patients (1 month to <4 years of age).

Patients in the two placebo-controlled trials were on 1 to 3 concomitant AEDs. In both of the trials, patients were stabilized on optimum dosages of their concomitant AEDs during an 8-week baseline phase. Patients who experienced at least 8 (minimum of 1 to 4 per month) partial seizures during the baseline phase were randomly assigned to placebo or to a specific dose of oxcarbazepine in addition to their other AEDs.

In these studies, the dose was increased over a two-week period until either the assigned dose was reached, or intolerance prevented increases. Patients then entered a 14 (pediatrics) or 24-week (adults) maintenance period.

In the adult trial, patients received fixed doses of 600, 1200 or 2400 mg/day. In the pediatric trial, patients received maintenance doses in the range of 30 to 46 mg/kg/day, depending on baseline weight. The primary measure of effectiveness in both trials was a between-group comparison of the percentage change in partial seizure frequency in the double-blind treatment phase relative to baseline phase. This comparison was statistically significant in favor of oxcarbazepine at all doses tested in both trials (p=0.0001 for all doses for both trials). The number of patients randomized to each dose, the median baseline seizure rate, and the median percentage seizure rate reduction for each trial are shown in Table 1. It is important to note that in the high-dose group in the study in adults, over 65% of patients discontinued treatment because of adverse events; only 46 (27%) of the patients in this group completed the 28-week study (see ADVERSE REACTIONS section), an outcome not seen in the monotherapy studies.

Table 1: Summary of Percentage Change in Partial Seizure Frequency from Baseline for Placebo-Controlled Adjunctive Therapy Trials
Trial | Treatment Group
 |  | N | Baseline Median Seizure Rate* | Median % Reduction
1 (pediatrics) | Oxcarbazepine | 136 | 12.5 | 34.8^1
 | Placebo | 128 | 13.1 | 9.4
2 (adults) | Oxcarbazepine 2400 mg/day | 174 | 10.0 | 49.9^1
 | Oxcarbazepine 1200 mg/day | 177 | 9.8 | 40.2^1
 | Oxcarbazepine 600 mg/day | 168 | 9.6 | 26.4^1
 | Placebo | 173 | 8.6 | 7.6

^1 p=0.0001; * = # per 28 days

Subset analyses of the antiepileptic efficacy of oxcarbazepine with regard to gender in these trials revealed no important differences in response between men and women. Because there were very few patients over the age of 65 in controlled trials, the effect of the drug in the elderly has not been adequately assessed.

The third adjunctive therapy trial enrolled 128 pediatric patients (1 month to <4 years of age) with inadequately-controlled partial seizures on 1 to 2 concomitant AEDs. Patients who experienced at least 2 study-specific seizures (i.e., electrographic partial seizures with a behavioral correlate) during the 72-hour baseline period were randomly assigned to either oxcarbazepine 10 mg/kg/day or were titrated up to 60 mg/kg/day within 26 days. Patients were maintained on their randomized target dose for 9 days and seizures were recorded through continuous video-EEG monitoring during the last 72 hours of the maintenance period. The primary measure of effectiveness in this trial was a between-group comparison of the change in seizure frequency per 24 hours compared to the seizure frequency at baseline. For the entire group of patients enrolled, this comparison was statistically significant in favor of oxcarbazepine 60 mg/kg/day. In this study, there was no evidence that oxcarbazepine was effective in patients below the age of 2 years (N=75).

INDICATIONS AND USAGE

Oxcarbazepine tablet is indicated for use as monotherapy or adjunctive therapy in the treatment of partial seizures in adults and as monotherapy in the treatment of partial seizures in children aged 4 years and above with epilepsy, and as adjunctive therapy in children aged 2 years and above with epilepsy.

CONTRAINDICATIONS

Oxcarbazepine tablets should not be used in patients with a known hypersensitivity to oxcarbazepine or to any of its components.

WARNINGS

Hyponatremia

Clinically significant hyponatremia (sodium <125 mmol/L) can develop during oxcarbazepine use. In the 14 controlled epilepsy studies 2.5% of oxcarbazepine treated patients (38/1,524) had a sodium of less than 125 mmol/L at some point during treatment, compared to no such patients assigned placebo or active control (carbamazepine and phenobarbital for adjunctive and monotherapy substitution studies, and phenytoin and valproate for the monotherapy initiation studies). Clinically significant hyponatremia generally occurred during the first three months of treatment with oxcarbazepine, although there were patients who first developed a serum sodium <125 mmol/L more than one year after initiation of therapy. Most patients who developed hyponatremia were asymptomatic but patients in the clinical trials were frequently monitored and some had their oxcarbazepine dose reduced, discontinued, or had their fluid intake restricted for hyponatremia. Whether or not these maneuvers prevented the occurrence of more severe events is unknown. Cases of symptomatic hyponatremia have been reported during post-marketing use. In clinical trials, patients whose treatment with oxcarbazepine was discontinued due to hyponatremia generally experienced normalization of serum sodium within a few days without additional treatment

Measurement of serum sodium levels should be considered for patients during maintenance treatment with oxcarbazepine, particularly if the patient is receiving other medications known to decrease serum sodium levels (for example, drugs associated with inappropriate ADH secretion) or if symptoms possibly indicating hyponatremia develop (e.g., nausea, malaise, headache, lethargy, confusion, obtundation, or increase in seizure frequency or severity).

Anaphylactic Reactions and Angioedema

Rare cases of anaphylaxis and angioedema involving the larynx, glottis, lips and eyelids have been reported in patients after taking the first or subsequent doses of oxcarbazepine. Angioedema associated with laryngeal edema can be fatal. If a patient develops any of these reactions after treatment with oxcarbazepine, the drug should be discontinued and an alternative treatment started. These patients should not be rechallenged with the drug (see WARNINGS, Patients with a Past History of Hypersensitivity Reaction to Carbamazepine subsection).

Patients with a Past History of Hypersensitivity Reaction to Carbamazepine

Patients who have had hypersensitivity reactions to carbamazepine should be informed that approximately 25% to 30% of them will experience hypersensitivity reactions with oxcarbazepine. For this reason patients should be specifically questioned about any prior experience with carbamazepine, and patients with a history of hypersensitivity reactions to carbamazepine should ordinarily be treated with oxcarbazepine only if the potential benefit justifies the potential risk. If signs or symptoms of hypersensitivity develop, oxcarbazepine should be discontinued immediately (see WARNINGS, Anaphylactic Reactions and Angioedema subsection; see PRECAUTIONS, Multi-Organ Hypersensitivity subsection).

Serious dermatological reactions, including Stevens-Johnson syndrome (SJS) and toxic epidermal necrolysis (TEN), have been reported in both children and adults in association with oxcarbazepine use. The median time of onset for reported cases was 19 days. Such serious skin reactions may be life threatening, and some patients have required hospitalization with very rare reports of fatal outcome. Recurrence of the serious skin reactions following re-challenge with oxcarbazepine has also been reported.

The reporting rate of TEN and SJS associated with oxcarbazepine use, which is generally accepted to be an underestimate due to underreporting, exceeds the background incidence rate estimates by a factor of 3- to 10-fold. Estimates of the background incidence rate for these serious skin reactions in the general population range between 0.5 to 6 cases per million-person years. Therefore, if a patient develops a skin reaction while taking oxcarbazepine tablets, consideration should be given to discontinuing oxcarbazepine use and prescribing another antiepileptic medication.

Suicidal Behavior and Ideation

Antiepileptic drugs (AEDs), including oxcarbazepine, increase the risk of suicidal thoughts or behavior in patients taking these drugs for any indication. Patients treated with any AED for any indication should be monitored for the emergence or worsening of depression, suicidal thoughts or behavior, and/or any unusual changes in mood or behavior.

Pooled analyses of 199 placebo-controlled clinical trials (mono- and adjunctive therapy) of 11 different AEDs showed that patients randomized to one of the AEDs had approximately twice the risk (adjusted Relative Risk 1.8, 95% CI:1.2, 2.7) of suicidal thinking or behavior compared to patients randomized to placebo. In these trials, which had a median treatment duration of 12 weeks, the estimated incidence rate of suicidal behavior or ideation among 27,863 AED-treated patients was 0.43%, compared to 0.24% among 16,029 placebo-treated patients, representing an increase of approximately one case of suicidal thinking or behavior for every 530 patients treated. There were four suicides in drug-treated patients in the trials and none in placebo-treated patients, but the number is too small to allow any conclusion about drug effect on suicide.

The increased risk of suicidal thoughts or behavior with AEDs was observed as early as one week after starting drug treatment with AEDs and persisted for the duration of treatment assessed. Because most trials included in the analysis did not extend beyond 24 weeks, the risk of suicidal thoughts or behavior beyond 24 weeks could not be assessed.

The risk of suicidal thoughts or behavior was generally consistent among drugs in the data analyzed. The finding of increased risk with AEDs of varying mechanisms of action and across a range of indications suggests that the risk applies to all AEDs used for any indication. The risk did not vary substantially by age (5 to 100 years) in the clinical trials analyzed. Table 2 shows absolute and relative risk by indication for all evaluated AEDs.

Table 2 Risk by Indication for Antiepileptic Drugs in the Pooled Analysis
Indication | Placebo Patients with Events Per 1,000 Patients | Drug Patients with Events Per 1,000 Patients | Relative Risk: Incidence of Events in Drug Patients/Incidence in Placebo Patients | Risk Difference: Additional Drug Patients with Events Per 1,000 Patients
Epilepsy | 1.0 | 3.4 | 3.5 | 2.4
Psychiatric | 5.7 | 8.5 | 1.5 | 2.9
Other | 1.0 | 1.8 | 1.9 | 0.9
Total | 2.4 | 4.3 | 1.8 | 1.9

The relative risk for suicidal thoughts or behavior was higher in clinical trials for epilepsy than in clinical trials for psychiatric or other conditions, but the absolute risk differences were similar for the epilepsy and psychiatric indications.

Anyone considering prescribing oxcarbazepine or any other AED must balance the risk of suicidal thoughts or behavior with the risk of untreated illness. Epilepsy and many other illnesses for which AEDs are prescribed are themselves associated with morbidity and mortality and an increased risk of suicidal thoughts and behavior. Should suicidal thoughts and behavior emerge during treatment, the prescriber needs to consider whether the emergence of these symptoms in any given patient may be related to the illness being treated.

Patients, their caregivers, and families should be informed that AEDs increase the risk of suicidal thoughts and behavior and should be advised of the need to be alert for the emergence or worsening of the signs and symptoms of depression, any unusual changes in mood or behavior, or the emergence of suicidal thoughts, behavior, or thoughts about self-harm. Behaviors of concern should be reported immediately to healthcare providers.

Withdrawal of AEDs

As with all antiepileptic drugs, oxcarbazepine should be withdrawn gradually to minimize the potential of increased seizure frequency.

PRECAUTIONS

Cognitive/Neuropsychiatric Adverse Events

Use of oxcarbazepine has been associated with central nervous system-related adverse events. The most significant of these can be classified into three general categories: 1) cognitive symptoms including psychomotor slowing, difficulty with concentration, and speech or language problems, 2) somnolence or fatigue, and 3) coordination abnormalities, including ataxia and gait disturbances.

Adult Patients

In one large, fixed-dose study, oxcarbazepine was added to existing AED therapy (up to three concomitant AEDs). By protocol, the dosage of the concomitant AEDs could not be reduced as oxcarbazepine was added, reduction in oxcarbazepine dosage was not allowed if intolerance developed, and patients were discontinued if unable to tolerate their highest target maintenance doses. In this trial, 65% of patients were discontinued because they could not tolerate the 2400 mg/day dose of oxcarbazepine on top of existing AEDs. The adverse events seen in this study were primarily CNS related and the risk for discontinuation was dose related.

In this trial, 7.1% of oxcarbazepine-treated patients and 4% of placebo-treated patients experienced a cognitive adverse event. The risk of discontinuation for these events was about 6.5 times greater on oxcarbazepine than on placebo. In addition, 26% of oxcarbazepine-treated patients and 12% of placebo-treated patients experienced somnolence. The risk of discontinuation for somnolence was about 10 times greater on oxcarbazepine than on placebo. Finally, 28.7% of oxcarbazepine-treated patients and 6.4% of placebo-treated patients experienced ataxia or gait disturbances. The risk for discontinuation for these events was about seven times greater on oxcarbazepine than on placebo.

In a single placebo-controlled monotherapy trial evaluating 2400 mg/day of oxcarbazepine, no patients in either treatment group discontinued double-blind treatment because of cognitive adverse events, somnolence, ataxia, or gait disturbance.

In the two dose-controlled conversion to monotherapy trials comparing 2400 mg/day and 300 mg/day oxcarbazepine, 1.1% of patients in the 2400 mg/day group discontinued double-blind treatment because of somnolence or cognitive adverse events compared to 0% in the 300 mg/day group. In these trials, no patients discontinued because of ataxia or gait disturbances in either treatment group.

Pediatric Patients

A study was conducted in pediatric patients (3 to 17 years old) with inadequately controlled partial seizures in which oxcarbazepine was added to existing AED therapy (up to two concomitant AEDs). By protocol, the dosage of concomitant AEDs could not be reduced as oxcarbazepine was added. Oxcarbazepine was titrated to reach a target dose ranging from 30 mg/kg to 46 mg/kg (based on a patient's body weight with fixed doses for predefined weight ranges).

Cognitive adverse events occurred in 5.8% of oxcarbazepine-treated patients (the single most common event being concentration impairment, 4 of 138 patients) and in 3.1% of patients treated with placebo. In addition, 34.8% of oxcarbazepine-treated patients and 14% of placebo-treated patients experienced somnolence. (No patient discontinued due to a cognitive adverse event or somnolence.). Finally, 23.2% of oxcarbazepine-treated patients and 7% of placebo-treated patients experienced ataxia or gait disturbances. Two (1.4%) oxcarbazepine-treated patients and 1 (0.8%) placebo-treated patient discontinued due to ataxia or gait disturbances.

Multi-organ hypersensitivity reactions have occurred in close temporal association (median time to detection 13 days: range 4 to 60) to the initiation of oxcarbazepine therapy in adult and pediatric patients. Although there have been a limited number of reports, many of these cases resulted in hospitalization and some were considered life threatening. Signs and symptoms of this disorder were diverse; however, patients typically, although not exclusively, presented with fever and rash associated with other organ system involvement. Other associated manifestations included lymphadenopathy, hepatitis, liver function test abnormalities, hematological abnormalities (e.g., eosinophilia, thrombocytopenia, neutropenia), pruritis, nephritis, oliguria, hepatorenal syndrome, arthralgia and asthenia. Because the disorder is variable in its expression, other organ system symptoms and signs, not noted here, may occur. If this reaction is suspected, oxcarbazepine tablets should be discontinued and an alternative treatment started. Although there are no case reports to indicate cross sensitivity with other drugs that produce this syndrome, the experience amongst drugs associated with multi-organ hypersensitivity would indicate this to be a possibility (see WARNINGS, Patients with a Past History of Hypersensitivity Reaction to Carbamazepine subsection).

Information for Patients

Anaphylactic reactions and angioedema may occur during treatment with oxcarbazepine. Patients should be advised to report immediately signs and symptoms suggesting angioedema (swelling of the face, eyes, lips, tongue or difficulty in swallowing or breathing) and to stop taking the drug until they have consulted with their physician (see WARNINGS, Anaphylactic Reactions and Angioedema subsection).

Patients who have exhibited hypersensitivity reactions to carbamazepine should be informed that approximately 25% to 30% of these patients may experience hypersensitivity reactions with oxcarbazepine. Patients should be advised that if they experience a hypersensitivity reaction while taking oxcarbazepine tablets they should consult with their physician immediately (see WARNINGS, Patients with a Past History of Hypersensitivity Reaction to Carbamazepine subsection).

Patients should be advised that serious skin reactions have been reported in association with oxcarbazepine. In the event a skin reaction should occur while taking oxcarbazepine, patients should consult with their physician immediately (see WARNINGS, Serious Dermatological Reactions subsection).

Patients should be instructed that a fever associated with other organ system involvement (rash, lymphadenopathy, etc.) may be drug related and should be reported to the physician immediately (see PRECAUTIONS, Multi-organ Hypersensitivity subsection).

Female patients of childbearing age should be warned that the concurrent use of oxcarbazepine with hormonal contraceptives may render this method of contraception less effective (see Drug Interactions subsection). Additional non-hormonal forms of contraception are recommended when using oxcarbazepine.

Patients, their caregivers, and families should be counseled that AEDs, including oxcarbazepine, may increase the risk of suicidal thoughts and behavior and should be advised of the need to be alert for the emergence or worsening of symptoms of depression, any unusual changes in mood or behavior, or the emergence of suicidal thoughts, behavior, or thoughts about self-harm. Behaviors of concern should be reported immediately to healthcare providers.

Caution should be exercised if alcohol is taken in combination with oxcarbazepine therapy, due to a possible additive sedative effect.

Patients should be advised that oxcarbazepine may cause dizziness and somnolence. Accordingly, patients should be advised not to drive or operate machinery until they have gained sufficient experience on oxcarbazepine to gauge whether it adversely affects their ability to drive or operate machinery.

Patients should be encouraged to enroll in the North American Antiepileptic Drug (NAAED) Pregnancy Registry if they become pregnant. This registry is collecting information about the safety of antiepileptic drugs during pregnancy. To enroll, patients can call the toll free number 1-888-233-2334 (see PRECAUTIONS, Pregnancy Category C subsection).

Laboratory Tests

Serum sodium levels below 125 mmol/L have been observed in patients treated with oxcarbazepine (see WARNINGS section). Experience from clinical trials indicates that serum sodium levels return toward normal when the oxcarbazepine dosage is reduced or discontinued, or when the patient was treated conservatively (e.g., fluid restriction).

Laboratory data from clinical trials suggest that oxcarbazepine use was associated with decreases in T4, without changes in T3 or TSH.

Drug Interactions

Oxcarbazepine can inhibit CYP2C19 and induce CYP3A4/5 with potentially important effects on plasma concentrations of other drugs. In addition, several AEDs that are cytochrome P450 inducers can decrease plasma concentrations of oxcarbazepine and MHD.

Oxcarbazepine was evaluated in human liver microsomes to determine its capacity to inhibit the major cytochrome P450 enzymes responsible for the metabolism of other drugs. Results demonstrate that oxcarbazepine and its pharmacologically active 10-monohydroxy metabolite (MHD) have little or no capacity to function as inhibitors for most of the human cytochrome P450 enzymes evaluated (CYP1A2, CYP2A6, CYP2C9, CYP2D6, CYP2E1, CYP4A9 and CYP4A11) with the exception of CYP2C19 and CYP3A4/5. Although inhibition of CYP3A4/5 by oxcarbazepine and MHD did occur at high concentrations, it is not likely to be of clinical significance. The inhibition of CYP2C19 by oxcarbazepine and MHD, however, is clinically relevant (see below).

In vitro, the UDP-glucuronyl transferase level was increased, indicating induction of this enzyme. Increases of 22% with MHD and 47% with oxcarbazepine were observed. As MHD, the predominant plasma substrate, is only a weak inducer of UDP-glucuronyl transferase, it is unlikely to have an effect on drugs that are mainly eliminated by conjugation through UDP-glucuronyl transferase (e.g., valproic acid, lamotrigine).

In addition, oxcarbazepine and MHD induce a subgroup of the cytochrome P450 3A family (CYP3A4 and CYP3A5) responsible for the metabolism of dihydropyridine calcium antagonists, oral contraceptives, resulting in a lower plasma concentration of these drugs.

As binding of MHD to plasma proteins is low (40%), clinically significant interactions with other drugs through competition for protein binding sites are unlikely.

Antiepileptic Drugs

Potential interactions between oxcarbazepine and other AEDs were assessed in clinical studies. The effect of these interactions on mean AUCs and Cmin are summarized in Table 3.

Table 3: Summary of AED Interactions with Oxcarbazepine
AED Coadministered | Dose of AED (mg/day) | Oxcarbazepine Dose (mg/day) | Influence of Oxcarbazepine on AED Concentration (Mean Change, 90% Confidence Interval) | Influence of AED on MHD Concentration (Mean Change, 90% Confidence Interval)
Carbamazepine | 400 to 2000 | 900 | nc^1 | 40% decrease [CI: 17% decrease, 57% decrease]
Phenobarbital | 100 to 150 | 600 to 1800 | 14% increase [CI: 2% increase, 24% increase] | 25% decrease [CI: 12% decrease, 51% decrease]
Phenytoin | 250 to 500 | 600 to 1800 >1200 to 2400 | nc^1,2 up to 40% increase^3 [CI: 12% increase, 60% increase] | 30% decrease [CI: 3% decrease, 48% decrease]
Valproic acid | 400 to 2800 | 600 to 1800 | nc^1 | 18% decrease [CI: 13% decrease, 40% decrease]

^1 nc denotes a mean change of less than 10%

^2 Pediatrics

^3 Mean increase in adults at high oxcarbazepine doses

In vivo, the plasma levels of phenytoin increased by up to 40% when oxcarbazepine was given at doses above 1200 mg/day. Therefore, when using doses of oxcarbazepine greater than 1200 mg/day during adjunctive therapy, a decrease in the dose of phenytoin may be required. The increase of phenobarbital level, however, is small (15%) when given with oxcarbazepine.

Strong inducers of cytochrome P450 enzymes (i.e., carbamazepine, phenytoin and phenobarbital) have been shown to decrease the plasma levels of MHD (29% to 40%).

No autoinduction has been observed with oxcarbazepine.

Hormonal Contraceptives

Coadministration of oxcarbazepine with an oral contraceptive has been shown to influence the plasma concentrations of the two hormonal components, ethinylestradiol (EE) and levonorgestrel (LNG). The mean AUC values of EE were decreased by 48% [90% CI: 22 to 65] in one study and 52% [90% CI: 38 to 52] in another study. The mean AUC values of LNG were decreased by 32% [90% CI: 20 to 45] in one study and 52% [90% CI: 42 to 52] in another study. Therefore, concurrent use of oxcarbazepine with hormonal contraceptives may render these contraceptives less effective (see Drug Interactions subsection). Studies with other oral or implant contraceptives have not been conducted.

Calcium Antagonists

After repeated coadministration of oxcarbazepine, the AUC of felodipine was lowered by 28% [90% CI: 20 to 33].

Verapamil produced a decrease of 20% [90% CI: 18 to 27] of the plasma levels of MHD.

Other Drug Interactions

Cimetidine, erythromycin and dextropropoxyphene had no effect on the pharmacokinetics of MHD. Results with warfarin show no evidence of interaction with either single or repeated doses of oxcarbazepine.

Drug/Laboratory Test Interactions

There are no known interactions of oxcarbazepine with commonly used laboratory tests.

Carcinogenesis/Mutagenesis/Impairment of Fertility

In two-year carcinogenicity studies, oxcarbazepine was administered in the diet at doses of up to 100 mg/kg/day to mice and by gavage at doses of up to 250 mg/kg to rats, and the pharmacologically active 10-hydroxy metabolite (MHD) was administered orally at doses of up to 600 mg/kg/day to rats. In mice, a dose-related increase in the incidence of hepatocellular adenomas was observed at oxcarbazepine doses ≥70 mg/kg/day or approximately 0.1 times the maximum recommended human dose (MRHD) on a mg/m^2 basis. In rats, the incidence of hepatocellular carcinomas was increased in females treated with oxcarbazepine at doses ≥25 mg/kg/day (0.1 times the MRHD on a mg/m^2 basis), and incidences of hepatocellular adenomas and/or carcinomas were increased in males and females treated with MHD at doses of 600 mg/kg/day (2.4 times the MRHD on a mg/m^2 basis) and ≥250 mg/kg/day (equivalent to the MRHD on a mg/m^2 basis), respectively. There was an increase in the incidence of benign testicular interstitial cell tumors in rats at 250 mg oxcarbazepine/kg/day and at ≥250 mg MHD/kg/day, and an increase in the incidence of granular cell tumors in the cervix and vagina in rats at 600 mg MHD/kg/day.

Oxcarbazepine increased mutation frequencies in the Ames test in vitro in the absence of metabolic activation in one of five bacterial strains. Both oxcarbazepine and MHD produced increases in chromosomal aberrations and polyploidy in the Chinese hamster ovary assay in vitro in the absence of metabolic activation. MHD was negative in the Ames test, and no mutagenic or clastogenic activity was found with either oxcarbazepine or MHD in V79 Chinese hamster cells in vitro. Oxcarbazepine and MHD were both negative for clastogenic or aneugenic effects (micronucleus formation) in an in vivo rat bone marrow assay.

In a fertility study in which rats were administered MHD (50, 150, or 450 mg/kg) orally prior to and during mating and early gestation, estrous cyclicity was disrupted and numbers of corpora lutea, implantations, and live embryos were reduced in females receiving the highest dose (approximately two times the MRHD on a mg/m^2 basis).

Pregnancy Category C

Increased incidences of fetal structural abnormalities and other manifestations of developmental toxicity (embryolethality, growth retardation) were observed in the offspring of animals treated with either oxcarbazepine or its active 10-hydroxy metabolite (MHD) during pregnancy at doses similar to the maximum recommended human dose.

When pregnant rats were given oxcarbazepine (30, 300, or 1000 mg/kg) orally throughout the period of organogenesis, increased incidences of fetal malformations (craniofacial, cardiovascular, and skeletal) and variations were observed at the intermediate and high doses (approximately 1.2 and 4 times, respectively, the maximum recommended human dose [MRHD] on a mg/m^2 basis). Increased embryofetal death and decreased fetal body weights were seen at the high dose. Doses ≥300 mg/kg were also maternally toxic (decreased body weight gain, clinical signs), but there is no evidence to suggest that teratogenicity was secondary to the maternal effects.

In a study in which pregnant rabbits were orally administered MHD (20, 100, or 200 mg/kg) during organogenesis, embryofetal mortality was increased at the highest dose (1.5 times the MRHD on a mg/m^2 basis). This dose produced only minimal maternal toxicity.

In a study in which female rats were dosed orally with oxcarbazepine (25, 50, or 150 mg/kg) during the latter part of gestation and throughout the lactation period, a persistent reduction in body weights and altered behavior (decreased activity) were observed in offspring exposed to the highest dose (0.6 times the MRHD on a mg/m^2 basis). Oral administration of MHD (25, 75, or 250 mg/kg) to rats during gestation and lactation resulted in a persistent reduction in offspring weights at the highest dose (equivalent to the MRHD on a mg/m^2 basis).

There are no adequate and well-controlled clinical studies of oxcarbazepine in pregnant women; however, oxcarbazepine is closely related structurally to carbamazepine, which is considered to be teratogenic in humans. Given this fact, and the results of the animal studies described, it is likely that oxcarbazepine is a human teratogen. Oxcarbazepine should be used during pregnancy only if the potential benefit justifies the potential risk to the fetus.

To provide information regarding the effects of in utero exposure to oxcarbazepine tablets, physicians are advised to recommend that pregnant patients taking oxcarbazepine tablets enroll in the NAAED Pregnancy Registry. This can be done by calling the toll free number 1-888-233-2334, and must be done by patients themselves. Information on the registry can also be found at the website http://www.aedpregnancyregistry.org/.

Labor and Delivery

The effect of oxcarbazepine on labor and delivery in humans has not been evaluated.

Nursing Mothers

Oxcarbazepine and its active metabolite (MHD) are excreted in human breast milk. A milk-to-plasma concentration ratio of 0.5 was found for both. Because of the potential for serious adverse reactions to oxcarbazepine in nursing infants, a decision should be made about whether to discontinue nursing or to discontinue the drug in nursing women, taking into account the importance of the drug to the mother.

Patients with Renal Impairment

In renally-impaired patients (creatinine clearance <30 mL/min), the elimination half-life of MHD is prolonged with a corresponding two-fold increase in AUC (see CLINICAL PHARMACOLOGY, Pharmacokinetics subsection). Oxcarbazepine therapy should be initiated at one-half the usual starting dose and increased, if necessary, at a slower than usual rate until the desired clinical response is achieved.

Pediatric Use

Oxcarbazepine is indicated for use as adjunctive therapy for partial seizures in patients aged 2 to 16 years. Oxcarbazepine is also indicated as monotherapy for partial seizures in patients aged 4 to 16 years. Oxcarbazepine has been given to 898 patients between the ages of 1 month to 17 years in controlled clinical trials (332 treated as monotherapy) and about 677 patients between the ages of 1 month to 17 years in other trials. (See ADVERSE REACTIONS section for a description of the adverse events associated with oxcarbazepine use in this population.)

Geriatric Use

There were 52 patients over age 65 in controlled clinical trials and 565 patients over the age of 65 in other trials. Following administration of single (300 mg) and multiple (600 mg/day) doses of oxcarbazepine in elderly volunteers (60 to 82 years of age), the maximum plasma concentrations and AUC values of MHD were 30% to 60% higher than in younger volunteers (18 to 32 years of age). Comparisons of creatinine clearance in young and elderly volunteers indicate that the difference was due to age-related reductions in creatinine clearance.

ADVERSE REACTIONS

Most Common Adverse Events in All Clinical Studies

Adjunctive Therapy/Monotherapy in Adults Previously Treated with other AEDs: The most commonly observed (≥5%) adverse experiences seen in association with oxcarbazepine and substantially more frequent than in placebo-treated patients were: Dizziness, somnolence, diplopia, fatigue, nausea, vomiting, ataxia, abnormal vision, abdominal pain, tremor, dyspepsia, abnormal gait.

Approximately 23% of these 1,537 adult patients discontinued treatment because of an adverse experience. The adverse experiences most commonly associated with discontinuation were: Dizziness (6.4%), diplopia (5.9%), ataxia (5.2%), vomiting (5.1%), nausea (4.9%), somnolence (3.8%), headache (2.9%), fatigue (2.1%), abnormal vision (2.1%), tremor (1.8%), abnormal gait (1.7%), rash (1.4%), hyponatremia (1%).

Monotherapy in Adults Not Previously Treated with other AEDs: The most commonly observed (≥5%) adverse experiences seen in association with oxcarbazepine in these patients were similar to those in previously treated patients.

Approximately 9% of these 295 adult patients discontinued treatment because of an adverse experience. The adverse experiences most commonly associated with discontinuation were: Dizziness (1.7%), nausea (1.7%), rash (1.7%), headache (1.4%).

Adjunctive Therapy/Monotherapy in Pediatric Patients 4 Years Old and Above Previously Treated with other AEDs: The most commonly observed (≥5%) adverse experiences seen in association with oxcarbazepine in these patients were similar to those seen in adults.

Approximately 11% of these 456 pediatric patients discontinued treatment because of an adverse experience. The adverse experiences most commonly associated with discontinuation were: Somnolence (2.4%), vomiting (2%), ataxia (1.8%), diplopia (1.3%), dizziness (1.3%), fatigue (1.1%), nystagmus (1.1%).

Monotherapy in Pediatric Patients 4 Years Old and Above Not Previously Treated with other AEDs: The most commonly observed (≥5%) adverse experiences seen in association with oxcarbazepine in these patients were similar to those in adults.

Approximately 9.2% of 152 pediatric patients discontinued treatment because of an adverse experience. The adverse experiences most commonly associated (≥1%) with discontinuation were rash (5.3%) and maculopapular rash (1.3%).

Adjunctive Therapy/Monotherapy in Pediatric Patients 1 Month to <4 Years Old Previously Treated or Not Previously Treated with other AEDs: The most commonly observed (≥5%) adverse experiences seen in association with oxcarbazepine in these patients were similar to those seen in older children and adults except for infections and infestations which were more frequently seen in these younger children.

Approximately 11% of these 241 pediatric patients discontinued treatment because of an adverse experience. The adverse experiences most commonly associated with discontinuation were: Convulsions (3.7%), status epilepticus (1.2%), and ataxia (1.2%).

Incidence in Controlled Clinical Studies: The prescriber should be aware that the figures in Tables 4, 5, 6 and 7 cannot be used to predict the frequency of adverse experiences in the course of usual medical practice where patient characteristics and other factors may differ from those prevailing during clinical studies. Similarly, the cited frequencies cannot be directly compared with figures obtained from other clinical investigations involving different treatments, uses, or investigators. An inspection of these frequencies, however, does provide the prescriber with one basis to estimate the relative contribution of drug and nondrug factors to the adverse event incidences in the population studied.

Controlled Clinical Studies of Adjunctive Therapy/Monotherapy in Adults Previously Treated with other AEDs:Table 4 lists treatment-emergent signs and symptoms that occurred in at least 2% of adult patients with epilepsy treated with oxcarbazepine or placebo as adjunctive treatment and were numerically more common in the patients treated with any dose of oxcarbazepine. Table 5 lists treatment-emergent signs and symptoms in patients converted from other AEDs to either high dose oxcarbazepine or low dose (300 mg) oxcarbazepine. Note that in some of these monotherapy studies patients who dropped out during a preliminary tolerability phase are not included in the tables.

Table 4: Treatment-Emergent Adverse Event Incidence in a Controlled Clinical Study of Adjunctive Therapy in Adults (Events in at Least 2% of Patients Treated with 2400 mg/day of Oxcarbazepine and Numerically More Frequent Than in the Placebo Group)
 | Oxcarbazepine Dosage (mg/day)
Body System/ Adverse Event | OXC 600 N=163 % | OXC 1200 N=171 % | OXC 2400 N=126 % | Placebo N=166 %
Body as a Whole
Fatigue | 15 | 12 | 15 | 7
Asthenia | 6 | 3 | 6 | 5
Edema Legs | 2 | 1 | 2 | 1
Weight Increase | 1 | 2 | 2 | 1
Feeling Abnormal | 0 | 1 | 2 | 0
Cardiovascular System
Hypotension | 0 | 1 | 2 | 0
Digestive System
Nausea | 15 | 25 | 29 | 10
Vomiting | 13 | 25 | 36 | 5
Pain Abdominal | 10 | 13 | 11 | 5
Diarrhea | 5 | 6 | 7 | 6
Dyspepsia | 5 | 5 | 6 | 2
Constipation | 2 | 2 | 6 | 4
Gastritis | 2 | 1 | 2 | 1
Metabolic and Nutritional Disorders
Hyponatremia | 3 | 1 | 2 | 1
Musculoskeletal System
Muscle Weakness | 1 | 2 | 2 | 0
Sprains and Strains | 0 | 2 | 2 | 1
Nervous System
Headache | 32 | 28 | 26 | 23
Dizziness | 26 | 32 | 49 | 13
Somnolence | 20 | 28 | 36 | 12
Ataxia | 9 | 17 | 31 | 5
Nystagmus | 7 | 20 | 26 | 5
Gait Abnormal | 5 | 10 | 17 | 1
Insomnia | 4 | 2 | 3 | 1
Tremor | 3 | 8 | 16 | 5
Nervousness | 2 | 4 | 2 | 1
Agitation | 1 | 1 | 2 | 1
Coordination Abnormal | 1 | 3 | 2 | 1
EEG Abnormal | 0 | 0 | 2 | 0
Speech Disorder | 1 | 1 | 3 | 0
Confusion | 1 | 1 | 2 | 1
Cranial Injury NOS | 1 | 0 | 2 | 1
Dysmetria | 1 | 2 | 3 | 0
Thinking Abnormal | 0 | 2 | 4 | 0
Respiratory System
Rhinitis | 2 | 4 | 5 | 4
Skin and Appendages
Acne | 1 | 2 | 2 | 0
Special Senses
Diplopia | 14 | 30 | 40 | 5
Vertigo | 6 | 12 | 15 | 2
Vision Abnormal | 6 | 14 | 13 | 4
Accommodation Abnormal | 0 | 0 | 2 | 0

Table 5: Treatment-Emergent Adverse Event Incidence in Controlled Clinical Studies of Monotherapy in Adults Previously Treated with Other AEDs (Events in at Least 2% of Patients Treated with 2400 mg/day of Oxcarbazepine and Numerically More Frequent Than in the Low Dose Control Group)
 | Oxcarbazepine Dosage (mg/day)
Body System/ Adverse Event | 2400 N=86 % | 300 N=86 %
Body as a Whole
Fatigue | 21 | 5
Fever | 3 | 0
Allergy | 2 | 0
Edema Generalized | 2 | 1
Pain Chest | 2 | 0
Digestive System
Nausea | 22 | 7
Vomiting | 15 | 5
Diarrhea | 7 | 5
Dyspepsia | 6 | 1
Anorexia | 5 | 3
Pain Abdominal | 5 | 3
Mouth Dry | 3 | 0
Hemorrhage Rectum | 2 | 0
Toothache | 2 | 1
Hemic and Lymphatic System
Lymphadenopathy | 2 | 0
Infections and Infestations
Infection Viral | 7 | 5
Infection | 2 | 0
Metabolic and Nutritional Disorders
Hyponatremia | 5 | 0
Thirst | 2 | 0
Nervous System
Headache | 31 | 15
Dizziness | 28 | 8
Somnolence | 19 | 5
Anxiety | 7 | 5
Ataxia | 7 | 1
Confusion | 7 | 0
Nervousness | 7 | 0
Insomnia | 6 | 3
Tremor | 6 | 3
Amnesia | 5 | 1
Convulsions Aggravated | 5 | 2
Emotional Lability | 3 | 2
Hypoesthesia | 3 | 1
Coordination Abnormal | 2 | 1
Nystagmus | 2 | 0
Speech Disorder | 2 | 0
Respiratory System
Upper Respiratory Tract Infection | 10 | 5
Coughing | 5 | 0
Bronchitis | 3 | 0
Pharyngitis | 3 | 0
Skin and Appendages
Hot Flushes | 2 | 1
Purpura | 2 | 0
Special Senses
Vision Abnormal | 14 | 2
Diplopia | 12 | 1
Taste Perversion | 5 | 0
Vertigo | 3 | 0
Earache | 2 | 1
Ear Infection NOS | 2 | 0
Urogenital and Reproductive System
Urinary Tract Infection | 5 | 1
Micturition Frequency | 2 | 1
Vaginitis | 2 | 0

Controlled Clinical Study of Monotherapy in Adults Not Previously Treated with other AEDs:Table 6 lists treatment-emergent signs and symptoms in a controlled clinical study of monotherapy in adults not previously treated with other AEDs that occurred in at least 2% of adult patients with epilepsy treated with oxcarbazepine or placebo and were numerically more common in the patients treated with oxcarbazepine.

Table 6: Treatment-Emergent Adverse Event Incidence in a Controlled Clinical Study of Monotherapy in Adults Not Previously Treated with Other AEDs (Events in at Least 2% of Patients Treated with Oxcarbazepine and Numerically More Frequent Than in the Placebo Group)
Body System/ Adverse Event | Oxcarbazepine N=55 % | Placebo N=49 %
Body as a Whole
Falling Down NOS | 4 | 0
Digestive System
Nausea | 16 | 12
Diarrhea | 7 | 2
Vomiting | 7 | 6
Constipation | 5 | 0
Dyspepsia | 5 | 4
Musculoskeletal System
Pain Back | 4 | 2
Nervous System
Dizziness | 22 | 6
Headache | 13 | 10
Ataxia | 5 | 0
Nervousness | 5 | 2
Amnesia | 4 | 2
Coordination Abnormal | 4 | 2
Tremor | 4 | 0
Respiratory System
Upper Respiratory Tract Infection | 7 | 0
Epistaxis | 4 | 0
Infection Chest | 4 | 0
Sinusitis | 4 | 2
Skin and Appendages
Rash | 4 | 2
Special Senses
Vision Abnormal | 4 | 0

Controlled Clinical Studies of Adjunctive Therapy/Monotherapy in Pediatric Patients Previously Treated with other AEDs: Table 7 lists treatment-emergent signs and symptoms that occurred in at least 2% of pediatric patients with epilepsy treated with oxcarbazepine or placebo as adjunctive treatment and were numerically more common in the patients treated with oxcarbazepine.

Table 7: Treatment-Emergent Adverse Event Incidence in Controlled Clinical Studies of Adjunctive Therapy/Monotherapy in Pediatric Patients Previously Treated with Other AEDs (Events in at Least 2% of Patients Treated with Oxcarbazepine and Numerically More Frequent Than in the Placebo Group)
Body System/ Adverse Event | Oxcarbazepine N=171 % | Placebo N=139 %
Body as a Whole
Fatigue | 13 | 9
Allergy | 2 | 0
Asthenia | 2 | 1
Digestive System
Vomiting | 33 | 14
Nausea | 19 | 5
Constipation | 4 | 1
Dyspepsia | 2 | 0
Nervous System
Headache | 31 | 19
Somnolence | 31 | 13
Dizziness | 28 | 8
Ataxia | 13 | 4
Nystagmus | 9 | 1
Emotional Lability | 8 | 4
Gait Abnormal | 8 | 3
Tremor | 6 | 4
Speech Disorder | 3 | 1
Concentration Impaired | 2 | 1
Convulsions | 2 | 1
Muscle Contractions Involuntary | 2 | 1
Respiratory System
Rhinitis | 10 | 9
Pneumonia | 2 | 1
Skin and Appendages
Bruising | 4 | 2
Sweating Increased | 3 | 0
Special Senses
Diplopia | 17 | 1
Vision Abnormal | 13 | 1
Vertigo | 2 | 0

Other Events Observed in Association with the Administration of Oxcarbazepine

In the paragraphs that follow, the adverse events, other than those in the preceding tables or text, that occurred in a total of 565 children and 1,574 adults exposed to oxcarbazepine and that are reasonably likely to be related to drug use are presented. Events common in the population, events reflecting chronic illness and events likely to reflect concomitant illness are omitted particularly if minor. They are listed in order of decreasing frequency. Because the reports cite events observed in open label and uncontrolled trials, the role of oxcarbazepine in their causation cannot be reliably determined.

Body as a Whole: Fever, malaise, pain chest precordial, rigors, weight decrease.

Cardiovascular System: Bradycardia, cardiac failure, cerebral hemorrhage, hypertension, hypotension postural, palpitation, syncope, tachycardia.

Digestive System: Appetite increased, blood in stool, cholelithiasis, colitis, duodenal ulcer, dysphagia, enteritis, eructation, esophagitis, flatulence, gastric ulcer, gingival bleeding, gum hyperplasia, hematemesis, hemorrhage rectum, hemorrhoids, hiccup, mouth dry, pain biliary, pain right hypochondrium, retching, sialoadenitis, stomatitis, stomatitis ulcerative.

Hemic and Lymphatic System: Leukopenia, thrombocytopenia.

Laboratory Abnormality: Gamma-GT increased, hyperglycemia, hypocalcemia, hypoglycemia, hypokalemia, liver enzymes elevated, serum transaminase increased.

Musculoskeletal System: Hypertonia muscle.

Nervous System: Aggressive reaction, amnesia, anguish, anxiety, apathy, aphasia, aura, convulsions aggravated, delirium, delusion, depressed level of consciousness, dysphonia, dystonia, emotional lability, euphoria, extrapyramidal disorder, feeling drunk, hemiplegia, hyperkinesia, hyperreflexia, hypoesthesia, hypokinesia, hyporeflexia, hypotonia, hysteria, libido decreased, libido increased, manic reaction, migraine, muscle contractions involuntary, nervousness, neuralgia, oculogyric crisis, panic disorder, paralysis, paroniria, personality disorder, psychosis, ptosis, stupor, tetany.

Respiratory System: Asthma, dyspnea, epistaxis, laryngismus, pleurisy.

Skin and Appendages: Acne, alopecia, angioedema, bruising, dermatitis contact, eczema, facial rash, flushing, folliculitis, heat rash, hot flushes, photosensitivity reaction, pruritus genital, psoriasis, purpura, rash erythematous, rash maculopapular, vitiligo, urticaria.

Special Senses: Accommodation abnormal, cataract, conjunctival hemorrhage, edema eye, hemianopia, mydriasis, otitis externa, photophobia, scotoma, taste perversion, tinnitus, xerophthalmia.

Surgical and Medical Procedures: Procedure dental oral, procedure female reproductive, procedure musculoskeletal, procedure skin.

Urogenital and Reproductive System: Dysuria, hematuria, intermenstrual bleeding, leukorrhea, menorrhagia, micturition frequency, pain renal, pain urinary tract, polyuria, priapism, renal calculus.

Other: Systemic lupus erythematosus.

Post-Marketing and Other Experience

The following adverse events not seen in controlled clinical trials have been observed in named patient programs or post-marketing experience:

Body as a Whole: Multi-organ hypersensitivity disorders characterized by features such as rash, fever, lymphadenopathy, abnormal liver function tests, eosinophilia and arthralgia (see PRECAUTIONS, Multi-Organ Hypersensitivity subsection).

Anaphylaxis (see WARNINGS, Anaphylactic Reactions and Angioedema subsection).

Skin and Appendages: Erythema multiforme, Stevens-Johnson syndrome, toxic epidermal necrolysis (see WARNINGS, Serious Dermatological Reactions subsection).

DRUG ABUSE AND DEPENDENCE

Abuse

The abuse potential of oxcarbazepine has not been evaluated in human studies.

Dependence

Intragastric injections of oxcarbazepine to four cynomolgus monkeys demonstrated no signs of physical dependence as measured by the desire to self-administer oxcarbazepine by lever pressing activity.

OVERDOSAGE

Human Overdose Experience

Isolated cases of overdose with oxcarbazepine have been reported. The maximum dose taken was approximately 24,000 mg. All patients recovered with symptomatic treatment.

Treatment and Management

There is no specific antidote. Symptomatic and supportive treatment should be administered as appropriate. Removal of the drug by gastric lavage and/or inactivation by administering activated charcoal should be considered.

DOSAGE AND ADMINISTRATION

Oxcarbazepine tablets are recommended as adjunctive treatment in the treatment of partial seizures in adults and children aged 2 to 16 years. Oxcarbazepine tablets are also recommended as monotherapy in the treatment of partial seizures in adults and children aged 4 to 16 years. All dosing should be given in a twice-a-day (BID) regimen. Oxcarbazepine oral suspension and oxcarbazepine film-coated tablets may be interchanged at equal doses.

Oxcarbazepine tablets should be kept out of the reach and sight of children.

Oxcarbazepine can be taken with or without food (see CLINICAL PHARMACOLOGY, Pharmacokinetics subsection).

Adults

Adjunctive Therapy

Treatment with oxcarbazepine should be initiated with a dose of 600 mg/day, given in a BID regimen. If clinically indicated, the dose may be increased by a maximum of 600 mg/day at approximately weekly intervals; the recommended daily dose is 1200 mg/day. Daily doses above 1200 mg/day show somewhat greater effectiveness in controlled trials, but most patients were not able to tolerate the 2400 mg/day dose, primarily because of CNS effects. It is recommended that the patient be observed closely and plasma levels of the concomitant AEDs be monitored during the period of oxcarbazepine titration, as these plasma levels may be altered, especially at oxcarbazepine doses greater than 1200 mg/day (see PRECAUTIONS, Drug Interactions subsection).

Conversion to Monotherapy

Patients receiving concomitant AEDs may be converted to monotherapy by initiating treatment with oxcarbazepine at 600 mg/day (given in a BID regimen) while simultaneously initiating the reduction of the dose of the concomitant AEDs. The concomitant AEDs should be completely withdrawn over 3 to 6 weeks, while the maximum dose of oxcarbazepine should be reached in about 2 to 4 weeks. Oxcarbazepine may be increased as clinically indicated by a maximum increment of 600 mg/day at approximately weekly intervals to achieve the recommended daily dose of 2400 mg/day. A daily dose of 1200 mg/day has been shown in one study to be effective in patients in whom monotherapy has been initiated with oxcarbazepine. Patients should be observed closely during this transition phase.

Initiation of Monotherapy

Patients not currently being treated with AEDs may have monotherapy initiated with oxcarbazepine. In these patients, oxcarbazepine should be initiated at a dose of 600 mg/day (given in a BID regimen); the dose should be increased by 300 mg/day every third day to a dose of 1200 mg/day. Controlled trials in these patients examined the effectiveness of a 1200 mg/day dose; a dose of 2400 mg/day has been shown to be effective in patients converted from other AEDs to oxcarbazepine monotherapy (see above).

Pediatric Patients

Adjunctive Therapy (Aged 2 to 16 Years)

In pediatric patients aged 4 to 16 years, treatment should be initiated at a daily dose of 8 to 10 mg/kg generally not to exceed 600 mg/day, given in a BID regimen. The target maintenance dose of oxcarbazepine should be achieved over two weeks, and is dependent upon patient weight, according to the following chart:

20 to 29 kg - 900 mg/day

29.1 to 39 kg - 1200 mg/day

>39 kg - 1800 mg/day

In the clinical trial, in which the intention was to reach these target doses, the median daily dose was 31 mg/kg with a range of 6 to 51 mg/kg.

In pediatric patients aged 2 to <4 years, treatment should also be initiated at a daily dose of 8 to 10 mg/kg generally not to exceed 600 mg/day, given in a BID regimen. For patients under 20 kg, a starting dose of 16 to 20 mg/kg may be considered (see CLINICAL PHARMACOLOGY). The maximum maintenance dose of oxcarbazepine should be achieved over 2 to 4 weeks and should not exceed 60 mg/kg/day in a BID regimen.

In the clinical trial in pediatric patients (2 to 4 years of age) in which the intention was to reach the target dose of 60 mg/kg/day, 50% of patients reached a final dose of at least 55 mg/kg/day.

Under adjunctive therapy (with and without enzyme-inducing AEDs), when normalized by body weight, apparent clearance (L/hr/kg) decreased when age increased such that children 2 to <4 years of age may require up to twice the oxcarbazepine dose per body weight compared to adults; and children 4 to ≤ 12 years of age may require a 50% higher oxcarbazepine dose per body weight compared to adults.

Conversion to Monotherapy (Aged 4 to 16 Years)

Patients receiving concomitant antiepileptic drugs may be converted to monotherapy by initiating treatment with oxcarbazepine tablets at approximately 8 to 10 mg/kg/day given in a BID regimen, while simultaneously initiating the reduction of the dose of the concomitant antiepileptic drugs. The concomitant antiepileptic drugs can be completely withdrawn over 3 to 6 weeks while oxcarbazepine may be increased as clinically indicated by a maximum increment of 10 mg/kg/day at approximately weekly intervals to achieve the recommended daily dose. Patients should be observed closely during this transition phase.

The recommended total daily dose of oxcarbazepine is shown in the table below.

Initiation of Monotherapy (Aged 4 to 16 Years)

Patients not currently being treated with antiepileptic drugs may have monotherapy initiated with oxcarbazepine. In these patients, oxcarbazepine should be initiated at a dose of 8 to 10 mg/kg/day given in a BID regimen. The dose should be increased by 5 mg/kg/day every third day to the recommended daily dose shown in the table below.

Table 8: Range of Maintenance Doses of Oxcarbazepine for Children by Weight During Monotherapy
 | From | To
Weight in kg | Dose (mg/day) | Dose (mg/day)
20 | 600 | 900
25 | 900 | 1200
30 | 900 | 1200
35 | 900 | 1500
40 | 900 | 1500
45 | 1200 | 1500
50 | 1200 | 1800
55 | 1200 | 1800
60 | 1200 | 2100
65 | 1200 | 2100
70 | 1500 | 2100

Patients with Hepatic Impairment

In general, dose adjustments are not required in patients with mild-to-moderate hepatic impairment (see CLINICAL PHARMACOLOGY, Pharmacokinetics, Special Populations subsection).

Patients with Renal Impairment

In patients with impaired renal function (creatinine clearance < 30 mL/min) oxcarbazepine therapy should be initiated at one-half the usual starting dose (300 mg/day) and increased slowly to achieve the desired clinical response (see CLINICAL PHARMACOLOGY, Pharmacokinetics, Special Populations subsection).

HOW SUPPLIED

150 mg Film-Coated Tablets: yellow colour, capsule shaped, biconvex, coated tablets scored and debossed with '183' on one side and scored on other side.

Bottle of 90: NDC 33261-0684-90

300 mg Film-Coated Tablets: yellow colour, capsule shaped, biconvex, coated tablets scored and debossed with '184' on one side and scored on other side.

Bottle of 60: NDC 33261-0841-60

Bottle of 90: NDC 33261-0841-90

600 mg Film-Coated Tablets: yellow colour, capsule shaped, biconvex, coated tablets scored and debossed with '185' on one side and scored on other side.

Bottle of 60: NDC 33261-0842-60

Store at 25°C (77°F); excursions permitted to 15°C-30°C (59°F-86°F) [see USP Controlled Room Temperature]. Dispense in tight container (USP).

Distributed by:
Caraco Pharmaceutical Laboratories, Ltd.
1150 Elijah McCoy Drive, Detroit, MI 48202

Manufactured by:
Sun Pharmaceutical Industries Ltd.
Acme Plaza, Andheri-Kurla Road,
Andheri (East), Mumbai- 400 059, India.

Repackaged By :
Aidarex Pharmaceuticals LLC,
Corona, CA 92880

ISS. 10/2009
PJPI0158A

PACKAGE LABEL.PRINCIPAL DISPLAY PANEL - Label - 150 mg

NDC 33261-0684-90
Oxcarbazepine Tablets
150 mg
Rx only
90 TABLETS

PACKAGE LABEL.PRINCIPAL DISPLAY PANEL - Label - 300 mg

NDC 33261-0841-90
Oxcarbazepine Tablets
300 mg
Rx only
90 TABLETS

PACKAGE LABEL.PRINCIPAL DISPLAY PANEL - Label - 600 mg

NDC 33261-0842-60
Oxcarbazepine Tablets
600 mg
Rx only
60 TABLETS